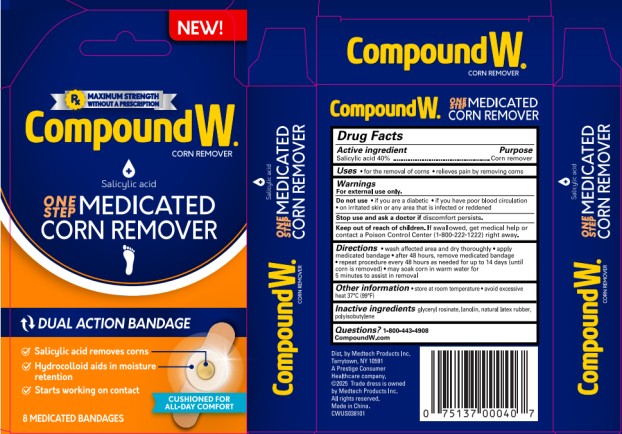 DRUG LABEL: Compound W One Step Medicated Corn Remover
NDC: 63029-621 | Form: PLASTER
Manufacturer: Medtech Products Inc.
Category: otc | Type: HUMAN OTC DRUG LABEL
Date: 20251009

ACTIVE INGREDIENTS: SALICYLIC ACID 0.4 g/1 1
INACTIVE INGREDIENTS: GLYCERYL ROSINATE; LANOLIN; NATURAL LATEX RUBBER; POLYISOBUTYLENE (1300 MW)

Compound W One Step Medicated Corn Remover 63029-621-08

Drug Facts

Active ingredient

Salicylic acid 40%

Purpose

Corn remover

Uses

• for the removal of corns • relieves pain by removing corns

Warnings

For external use only.

Do not use

• if you are a diabetic • if you have poor blood circulation • on irritated

skin or any area that is infected or reddened.

Stop use and ask a doctor if

discomfort persists.

Keep out of reach of children.

If swallowed, get medical help or contact a Poison Control Center (1-800-222-1222) right away.

Directions

• wash affected area and dry thoroughly • apply medicated bandage

• after 48 hours, remove medicated bandage • repeat procedure every 48 hours as

needed for up to 14 days (until corn is removed) • may soak corn in warm water for

5 minutes to assist in removal

Other information

- store at room temperature
- avoid excessive heat 37°C (99°F)

Inactive ingredients:

glyceryl rosinate, lanolin, natural rubber, polyisobutylene

Questions?

1-800-443-4908

CompoundW.com

Dist. by Medtech Products Inc.
Tarrytown, NY 10591
A Prestige Consumer Healthcare
company. ©2025 Trade dress is owned
by Medtech Products Inc. All rights
reserved. Made in China.
CWUS038101

Principal Display Panel

Compound W
CORN REMOVER
Salicylic acid
ONE STEP MEDICATED
CORN REMOVER
8 MEDICATED BANDAGES